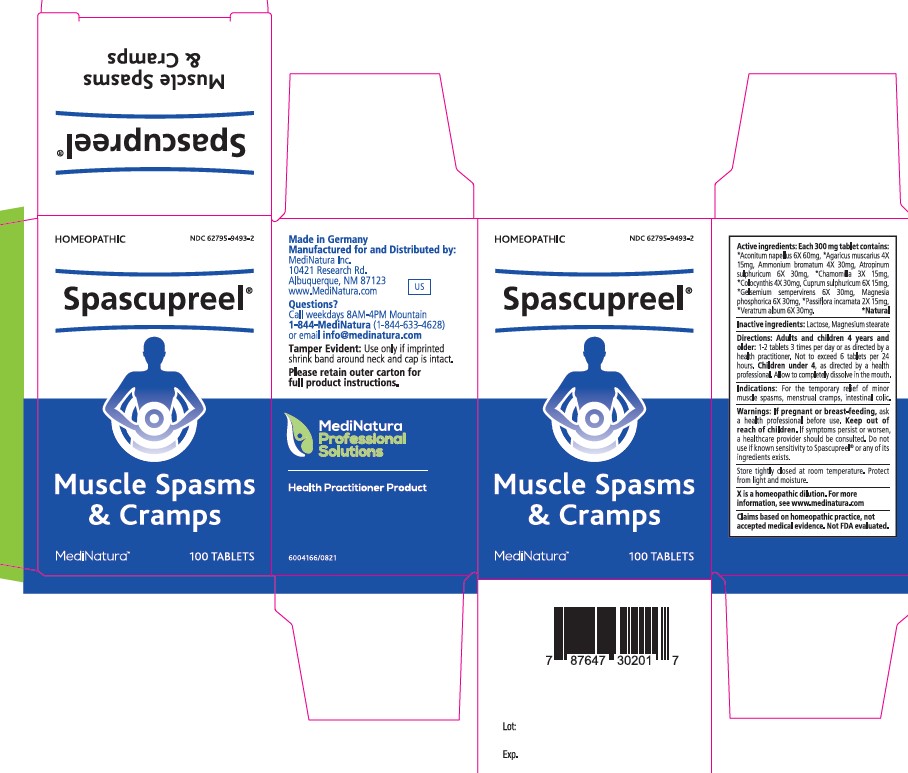 DRUG LABEL: Spascupreel
NDC: 62795-9493 | Form: TABLET
Manufacturer: MediNatura Inc
Category: homeopathic | Type: HUMAN OTC DRUG LABEL
Date: 20230510

ACTIVE INGREDIENTS: ACONITUM NAPELLUS WHOLE 6 [hp_X]/1 1; AMANITA MUSCARIA FRUITING BODY 4 [hp_X]/1 1; AMMONIUM BROMIDE 4 [hp_X]/1 1; ATROPINE SULFATE 6 [hp_X]/1 1; MATRICARIA CHAMOMILLA WHOLE 3 [hp_X]/1 1; CITRULLUS COLOCYNTHIS FRUIT PULP 4 [hp_X]/1 1; CUPRIC SULFATE 6 [hp_X]/1 1; GELSEMIUM SEMPERVIRENS ROOT 6 [hp_X]/1 1; MAGNESIUM PHOSPHATE, DIBASIC TRIHYDRATE 6 [hp_X]/1 1; PASSIFLORA INCARNATA FLOWERING TOP 2 [hp_X]/1 1; VERATRUM ALBUM ROOT 6 [hp_X]/1 1
INACTIVE INGREDIENTS: LACTOSE, UNSPECIFIED FORM; MAGNESIUM STEARATE

Spascupreel

Indications:

For the temporary relief of minor
muscle spasms, menstrual cramps, intestinal colic.

Warnings:

If pregnant or breast-feeding, ask
a health professional before use. Keep out of
reach of children. If symptoms persist or worsen,
a healthcare provider should be consulted. Do not
use if known sensitivity to Spascupreel® or any of its
ingredients exists.

Directions:

Adults and children 4 years and
older: 1-2 tablets 3 times per day or as directed by a
health practitioner. Not to exceed 6 tablets per 24
hours. Children under 4, as directed by a health
professional. Allow to completely dissolve in the mouth.

Inactive ingredients:

Lactose, Magnesium stearate

KEEP OUT OF REACH OF CHILDREN

Purpose

Muscle Spasms
& Cramps

Active ingredients:

Each 300 mg tablet contains:
*Aconitum napellus 6X 60mg, *Agaricus muscarius 4X
15mg, Ammonium bromatum 4X 30mg, Atropinum
sulphuricum 6X 30mg, *Chamomilla 3X 15mg,
*Colocynthis 4X 30mg, Cuprum sulphuricum 6X 15mg,
*Gelsemium sempervirens 6X 30mg, Magnesia
phosphorica 6X 30mg, *Passiflora incarnata 2X 15mg,
*Veratrum album 6X 30mg. *Natural